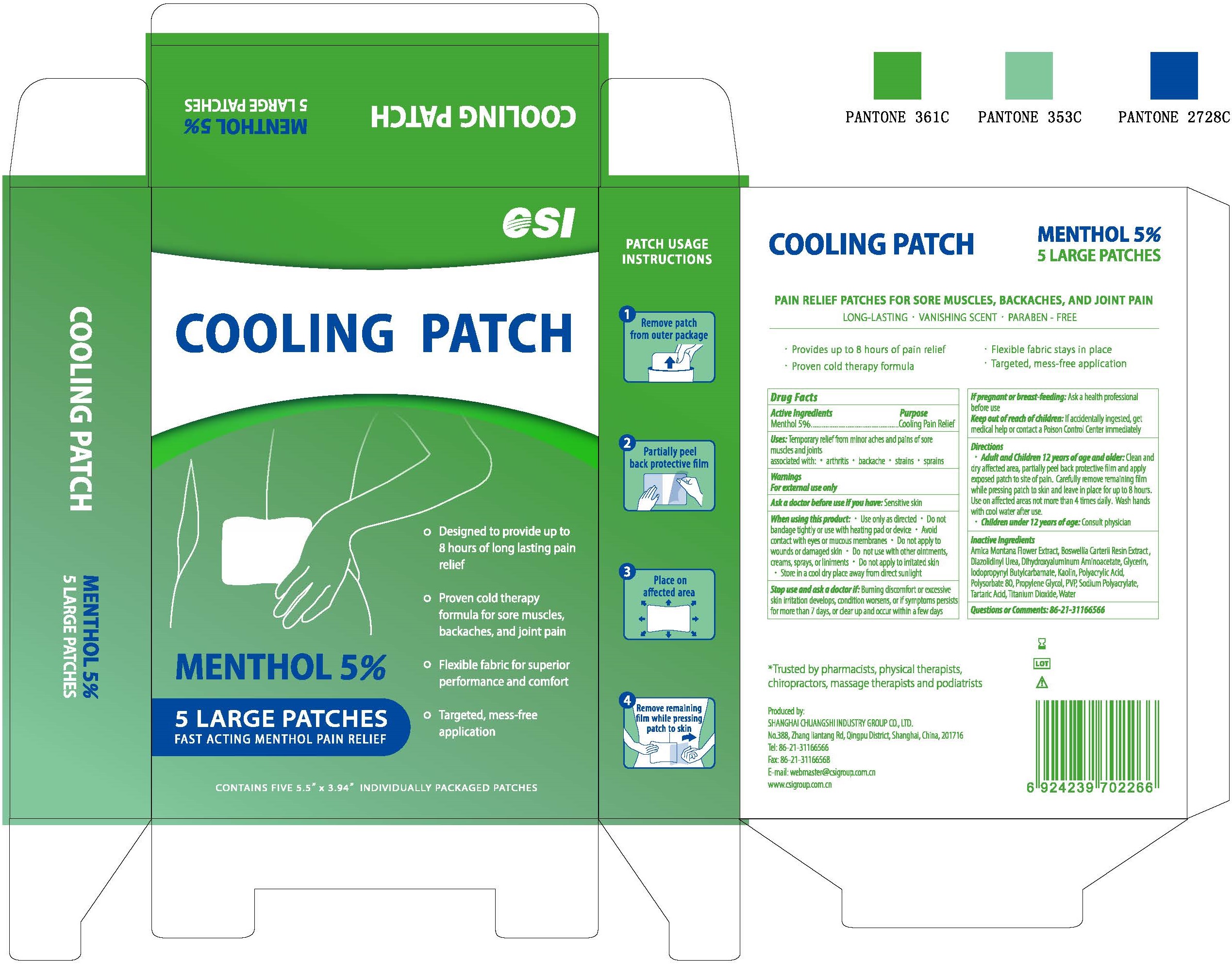 DRUG LABEL: CSI Cooling Patch
NDC: 73557-135 | Form: TAPE
Manufacturer: Shanghai Chuangshi Industry Group Co., Ltd
Category: otc | Type: HUMAN OTC DRUG LABEL
Date: 20200603

ACTIVE INGREDIENTS: MENTHOL 0.05 g/1 g
INACTIVE INGREDIENTS: GLYCERIN 0.25 g/1 g; POLYSORBATE 80 0.004 g/1 g; POVIDONE K30 0.05 g/1 g; GREEN TEA LEAF 0.001 g/1 g; ALOE VERA LEAF 0.002 g/1 g; DIAZOLIDINYL UREA 0.0015 g/1 g; ARNICA MONTANA FLOWER 0.002 g/1 g; FRANKINCENSE 0.001 g/1 g; KAOLIN 0.005 g/1 g; TARTARIC ACID 0.0025 g/1 g; WATER 0.3474 g/1 g; DIHYDROXYALUMINUM AMINOACETATE 0.0011 g/1 g; PROPYLENE GLYCOL 0.05 g/1 g; POLYACRYLIC ACID (250000 MW) 0.17 g/1 g; IODOPROPYNYL BUTYLCARBAMATE 0.0015 g/1 g; SODIUM POLYACRYLATE (8000 MW) 0.06 g/1 g; TITANIUM DIOXIDE 0.001 g/1 g

CSI Cooling Patch, 5 Large Patches

Active ingredient

Menthol

Inactive ingredient

Aloe barbadensis leaf extract
Arnica montana flower extract
Boswellia carterii resin extract
Camellia sinensis leaf extract
Diazolidinyl urea
Dihydroxyaluminun aminoacetate
Glycerin
Iodopropynyl butylcarbamate
Kaolin
Polyacrylic acid
Polysorbate 80
Propylene glycol
Pvp
Sodium polyacrylate
Tartaric acid
Titanium dioxide
Water

Purpose

Pain relief with cold therapy for sore muscles, backaches, and joint pain.

When using

Temporary relief from minor aches and pains of sore muscles and joints associated with arthritis, backache, strains, sprains.

Stop use

Buming discomfort or excessive skin irritation develops, condition worsens, or if symptoms persists for more than 7 days, or clear up and occur within few days.

Ask doctor

Buming discomfort or excessive skin irritation develops, condition worsens, or if symptoms persists for more than 7 days, or clear up and occur within few days.

If pregnant or breast-feeding.

Ask doctor/pharmacist

Buming discomfort or excessive skin irritation develops, condition worsens, or if symptoms persists for more than 7 days, or clear up and occur within few days.
If pregnant or breast-feeding.

Keep out of reach of children

If accidentally ingested, get medical help or contact a Poison Control Center immediately.

Questions

Please contact with us at the phone number +86-21-31166566 or email webmaster@csigroup.com.cn when you have any questions.

Pregnancy or breast feeding

Pregnant or breast feeding women shall follow doctor advice.

Indications & usage

* Adult and Children 12 year of age and older:
Clean and dry affected area, partially peel back protective film and apply exposed patch to site of pain. Carefully remove remaining film while pressing patch to skin and leave in place for up to 8 hours. Use on affected areas not more than 4 times daily. Wash hands with cool water after use.
* Children under 12 years of age:
Consult physician.

Dosage & administration

One patch at a time. Use it as needed, no more than 4 times daily.

For external use only.

Dosage forms & strengths

This is a patch, tape dosage form.

The active ingredient strength is 5%.

Warnings

For external use only.
Use only as directed.
Store in a cool dry place away from direct sunlight.

Package label. Principal display panel

Package